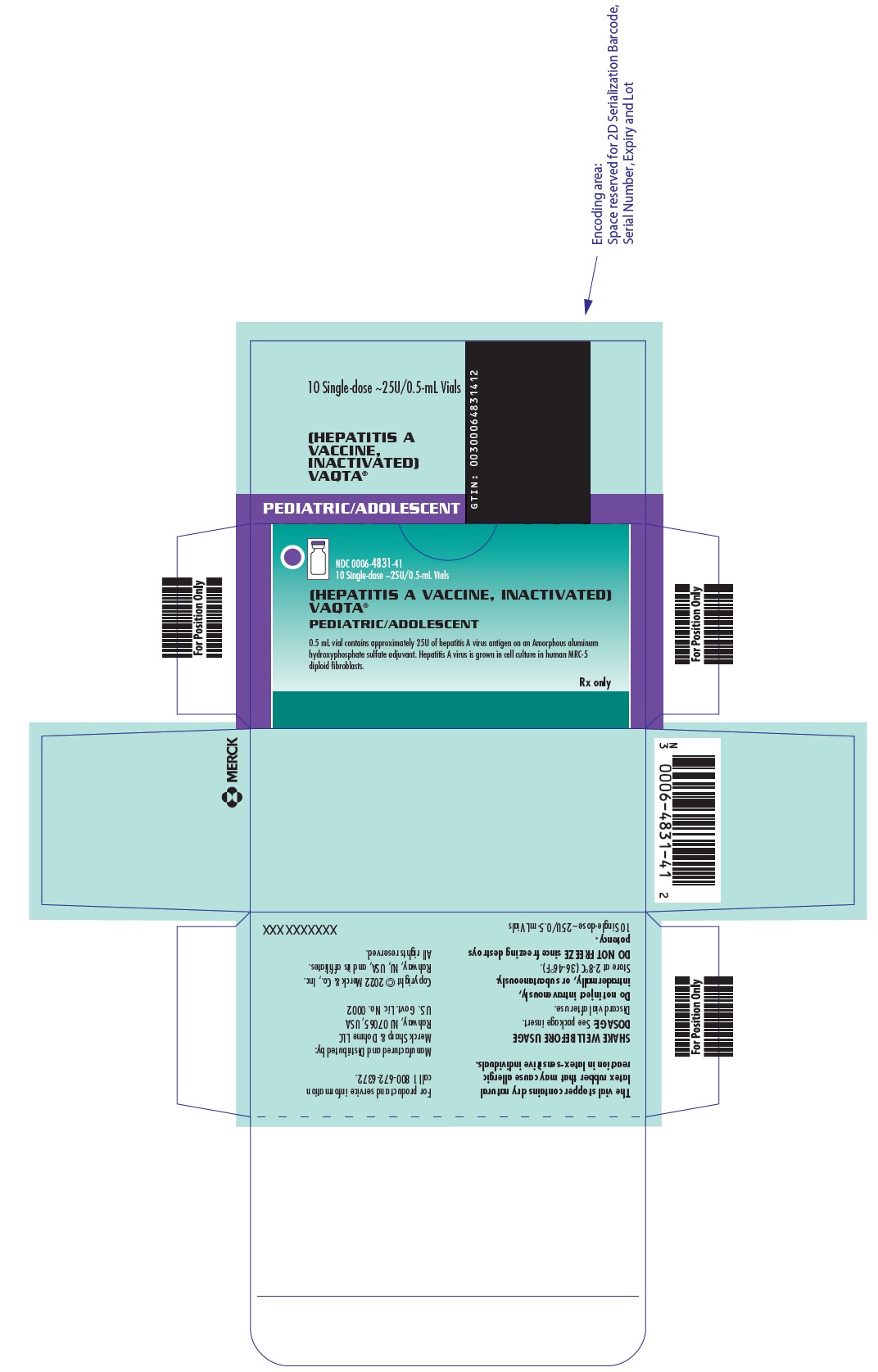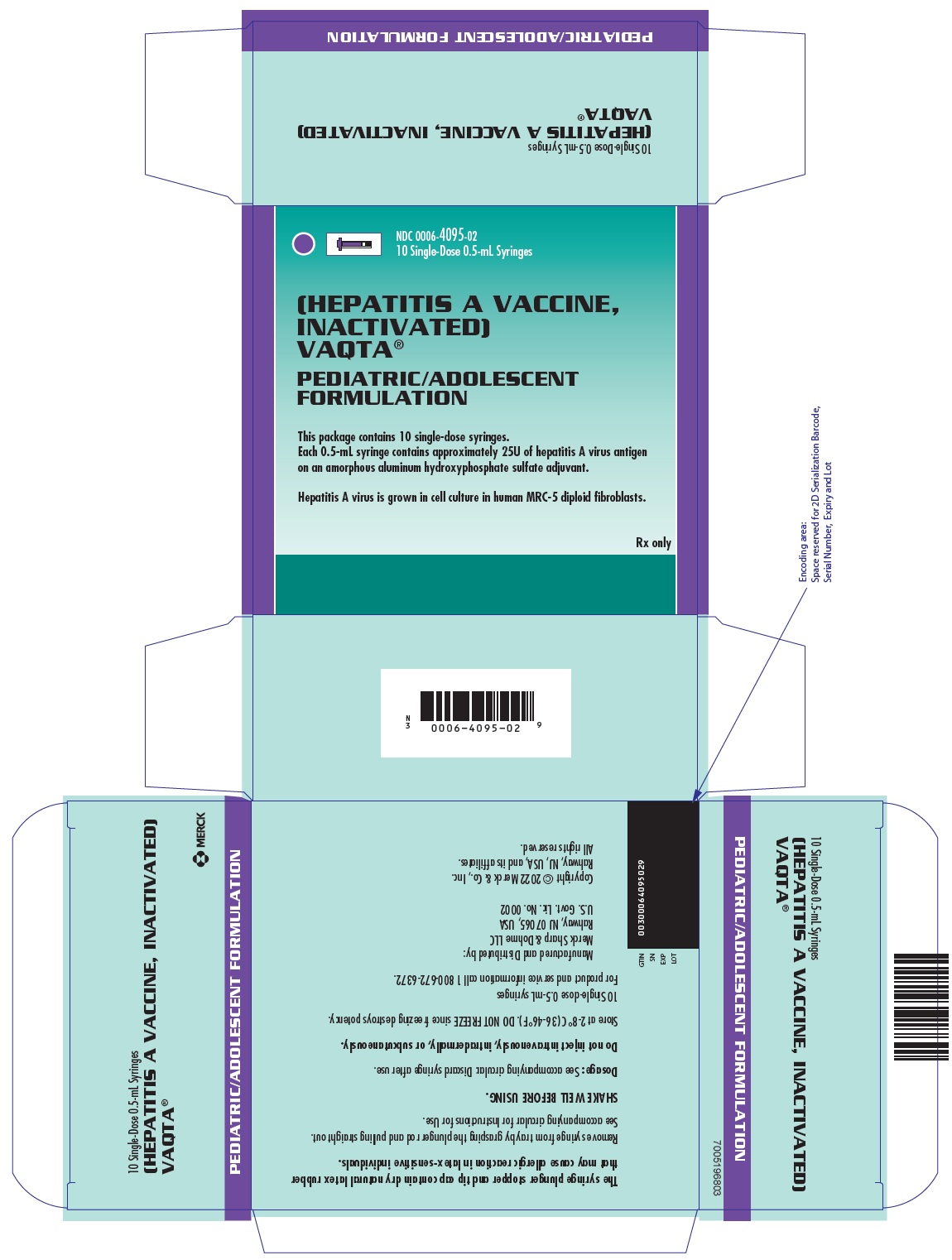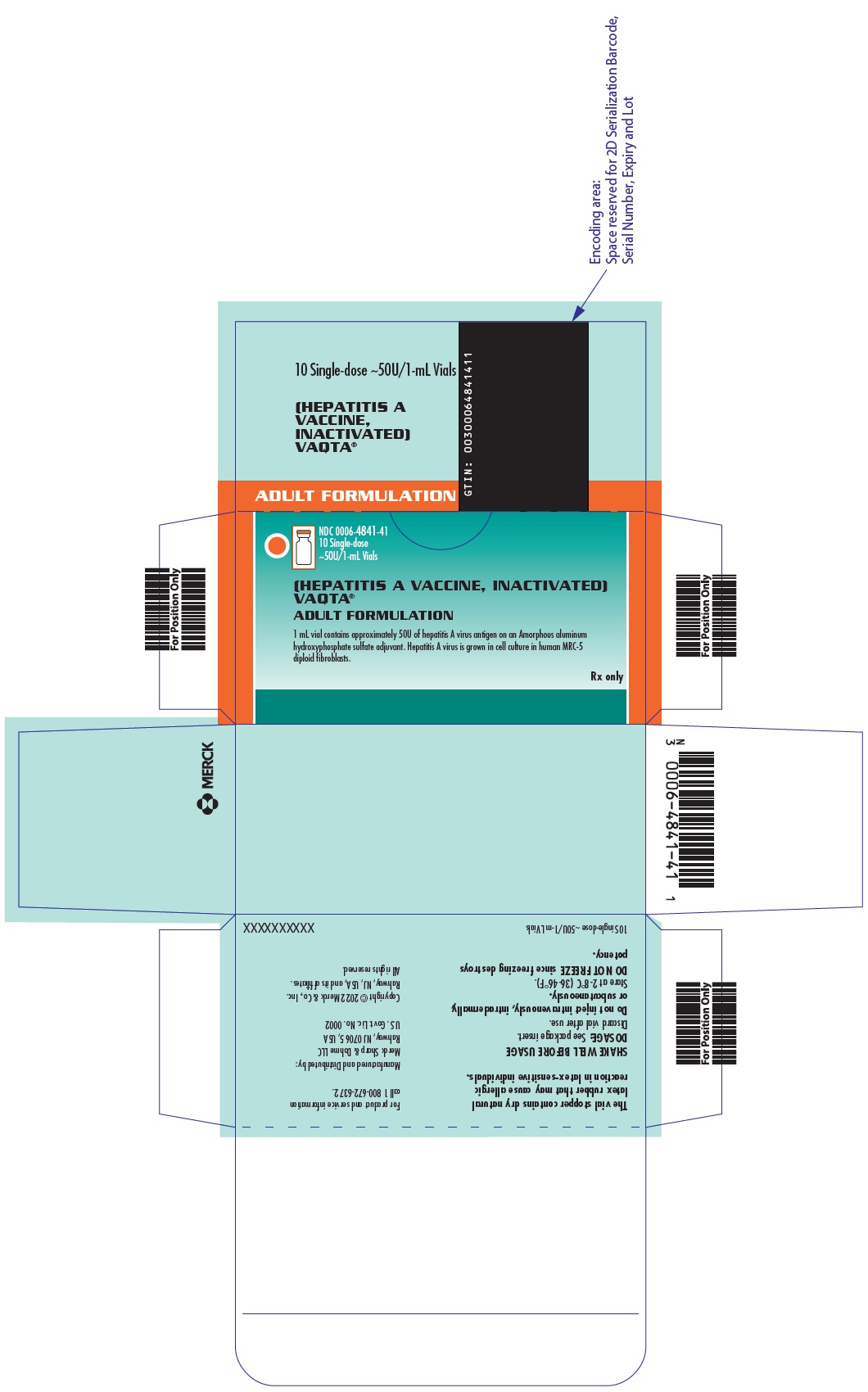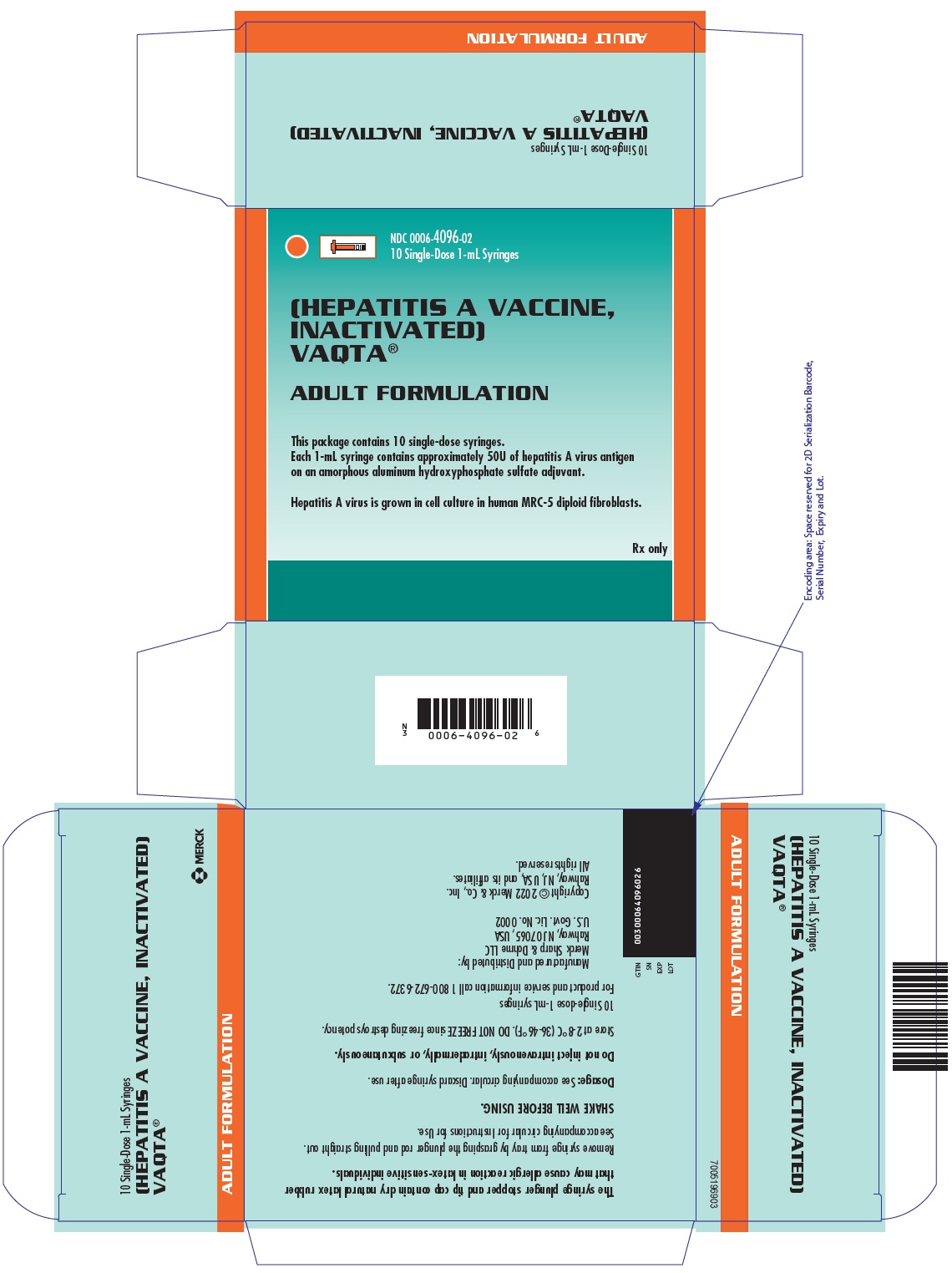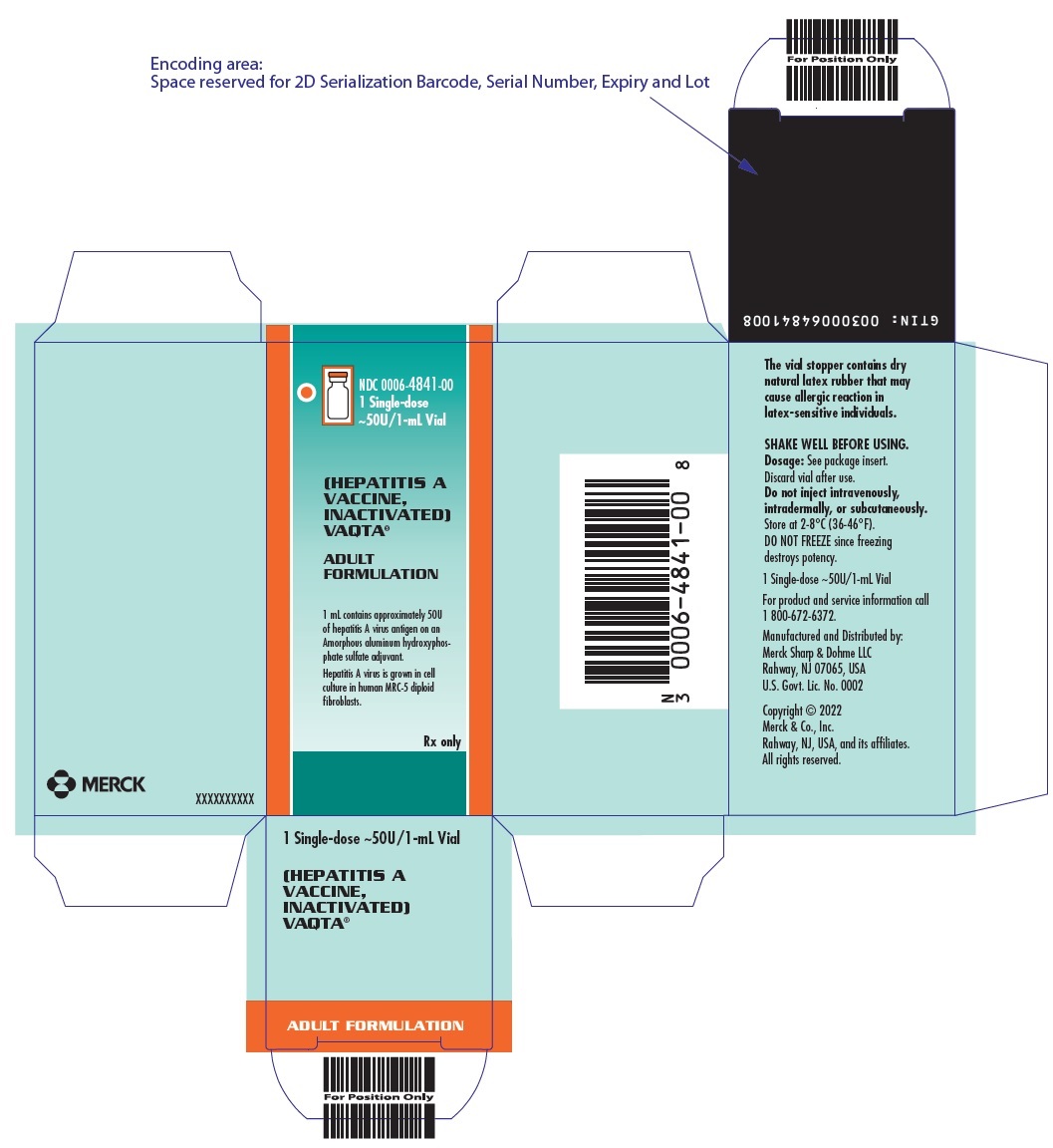 DRUG LABEL: VAQTA
NDC: 0006-4831 | Form: INJECTION, SUSPENSION
Manufacturer: Merck Sharp & Dohme LLC
Category: other | Type: VACCINE LABEL
Date: 20250916

ACTIVE INGREDIENTS: HEPATITIS A VIRUS STRAIN CR 326F ANTIGEN (FORMALDEHYDE INACTIVATED) 25 [iU]/0.5 mL
INACTIVE INGREDIENTS: SODIUM BORATE 35 ug/0.5 mL; SODIUM CHLORIDE; WATER

HIGHLIGHTS OF PRESCRIBING INFORMATION

These highlights do not include all the information needed to use VAQTA safely and effectively. See full prescribing information for VAQTA.
VAQTA® (Hepatitis A Vaccine, Inactivated)
Suspension for Intramuscular Injection
Initial U.S. Approval: 1996

RECENT MAJOR CHANGES

Warnings and Precautions (5.2) | 09/2025

1 INDICATIONS AND USAGE

VAQTA is a vaccine indicated for the prevention of disease caused by hepatitis A virus (HAV) in persons 12 months of age and older. The primary dose should be given at least 2 weeks prior to expected exposure to HAV. (1.1)

2 DOSAGE AND ADMINISTRATION

- For intramuscular administration only. (2)
- Children/Adolescents: vaccination consists of a 0.5-mL primary dose administered intramuscularly, and a 0.5-mL booster dose administered intramuscularly 6 to 18 months later. (2.1)
- Adults: vaccination consists of a 1-mL primary dose administered intramuscularly, and a 1-mL booster dose administered intramuscularly 6 to 18 months later. (2.1)

3 DOSAGE FORMS AND STRENGTHS

Suspension supplied in four presentations:

- 0.5-mL pediatric dose in single-dose vials and prefilled syringes. (3, 11, 16)
- 1-mL adult dose in single-dose vials and prefilled syringes. (3, 11, 16)

4 CONTRAINDICATIONS

Do not administer VAQTA to individuals with a history of immediate and/or severe allergic or hypersensitivity reactions (e.g., anaphylaxis) after a previous dose of any hepatitis A vaccine or with an anaphylactic reaction to neomycin. (4, 11)

5 WARNINGS AND PRECAUTIONS

- The vial stopper contains dry natural latex rubber that may cause allergic reactions in latex-sensitive individuals. (5.2)

6 ADVERSE REACTIONS

The most common local adverse reactions and systemic adverse events (≥15%) reported in different clinical trials across different age groups when VAQTA was administered alone or concomitantly were:

- Children — 12 through 23 months of age: injection-site pain/tenderness (37.0%), injection-site erythema (21.2%), fever (16.4% when administered alone, and 27.0% when administered concomitantly) (6.1)
- Children/Adolescents — 2 through 18 years of age: injection-site pain (18.7%) (6.1)
- Adults — 19 years of age and older: injection-site pain, tenderness, or soreness (67.0%), injection-site warmth (18.2%) and headache (16.1%) (6.1)

To report SUSPECTED ADVERSE REACTIONS, contact Merck Sharp & Dohme LLC at 1-877-888-4231 or VAERS at 1-800-822-7967 or www.vaers.hhs.gov .

7 DRUG INTERACTIONS

- Do not mix VAQTA with any other vaccine in the same syringe or vial. (7.1)

FULL PRESCRIBING INFORMATION

1 INDICATIONS AND USAGE

1.1 Indications and Use

VAQTA® [Hepatitis A Vaccine, Inactivated] is indicated for the prevention of disease caused by hepatitis A virus (HAV) in persons 12 months of age and older. The primary dose should be given at least 2 weeks prior to expected exposure to HAV.

2 DOSAGE AND ADMINISTRATION

FOR INTRAMUSCULAR ADMINISTRATION ONLY.

2.1 Dosage and Schedule

Children/Adolescents (12 months through 18 years of age): The vaccination schedule consists of a primary 0.5-mL dose administered intramuscularly, and a 0.5-mL booster dose administered intramuscularly 6 to 18 months later.

Adults (19 years of age and older): The vaccination schedule consists of a primary 1-mL dose administered intramuscularly, and a 1-mL booster dose administered intramuscularly 6 to 18 months later.

Booster Immunization Following Another Manufacturer's Hepatitis A Vaccine: A booster dose of VAQTA may be given at 6 to 12 months following a primary dose of HAVRIX [see Clinical Studies (14.6)].

2.2 Preparation and Administration

Shake the single-dose vial or single-dose prefilled syringe well to obtain a slightly opaque, white suspension before withdrawal and use. Parenteral drug products should be inspected visually for particulate matter and discoloration prior to administration, whenever solution and container permit. Discard if the suspension does not appear homogenous or if extraneous particulate matter remains or discoloration is observed.

For single-dose vials, withdraw and administer entire dose of VAQTA intramuscularly using a sterile needle and syringe. Discard vial after use.

For single-dose prefilled syringes, securely attach a needle by twisting in a clockwise direction and administer dose of VAQTA intramuscularly. Discard syringe after use.

For adults, adolescents, and children older than 2 years of age, the deltoid muscle is the preferred site for intramuscular injection. For children 12 through 23 months of age, the anterolateral area of the thigh is the preferred site for intramuscular injection.

3 DOSAGE FORMS AND STRENGTHS

Suspension for injection available in four presentations:

- 0.5-mL pediatric dose in single-dose vials and prefilled syringes
- 1-mL adult dose in single-dose vials and prefilled syringes

[See Description (11) for listing of vaccine components and How Supplied/Storage and Handling (16).]

4 CONTRAINDICATIONS

Do not administer VAQTA to individuals with a history of immediate and/or severe allergic or hypersensitivity reactions (e.g., anaphylaxis) after a previous dose of any hepatitis A vaccine, or to individuals who have had an anaphylactic reaction to any component of VAQTA, including neomycin [see Description (11)].

5 WARNINGS AND PRECAUTIONS

5.1 Prevention and Management of Allergic Vaccine Reactions

Appropriate medical treatment and supervision must be available to manage possible anaphylactic reactions following administration of the vaccine [see Contraindications (4)].

5.2 Hypersensitivity to Latex

The vial stopper contains dry natural latex rubber that may cause allergic reactions in latex-sensitive individuals [see How Supplied/Storage and Handling (16)].

5.3 Altered Immunocompetence

Immunocompromised persons, including individuals receiving immunosuppressive therapy, may have a diminished immune response to VAQTA and may not be protected against HAV infection after vaccination [see Use in Specific Populations (8.6)].

5.4 Limitations of Vaccine Effectiveness

Hepatitis A virus has a relatively long incubation period (approximately 20 to 50 days). VAQTA may not prevent hepatitis A infection in individuals who have an unrecognized hepatitis A infection at the time of vaccination. Vaccination with VAQTA may not result in a protective response in all susceptible vaccinees.

6 ADVERSE REACTIONS

6.1 Clinical Trials Experience

Because clinical trials are conducted under widely varying conditions, adverse reaction rates observed in the clinical trials of a vaccine cannot be directly compared to rates in the clinical trials of another vaccine and may not reflect the rates observed in practice.

The safety of VAQTA has been evaluated in over 10,000 subjects 1 year to 85 years of age. Subjects were given one or two doses of the vaccine. The second (booster dose) was given 6 months or more after the first dose.

The most common local adverse reactions and systemic adverse events (≥15%) reported in different clinical trials across different age groups when VAQTA was administered alone or concomitantly were:

- Children — 12 through 23 months of age: injection-site pain/tenderness (37.0%), injection-site erythema (21.2%), fever (16.4% when administered alone, and 27.0% when administered concomitantly).
- Children/Adolescents — 2 through 18 years of age: injection-site pain (18.7%)
- Adults — 19 years of age and older: injection-site pain, tenderness, or soreness (67.0%), injection-site warmth (18.2%) and headache (16.1%)

Allergic Reactions

Local and/or systemic allergic reactions that occurred in <1% of over 10,000 children/adolescents or adults in clinical trials regardless of causality included: injection-site pruritus and/or rash; bronchial constriction; asthma; wheezing; edema/swelling; rash; generalized erythema; urticaria; pruritus; eye irritation/itching; dermatitis [see Contraindications (4) and Warnings and Precautions (5.1)].

Children — 12 through 23 Months of Age

Across five clinical trials, 4374 children 12 to 23 months of age received one or two 25U doses of VAQTA, including 3885 children who received 2 doses of VAQTA and 1250 children who received VAQTA concomitantly with one or more other vaccines, including Measles, Mumps, and Rubella Virus Vaccine, Live (M-M-R II®), Varicella Vaccine, Live (VARIVAX®), Diphtheria and Tetanus Toxoids and Acellular Pertussis Vaccine, Adsorbed (Tripedia or INFANRIX), Measles, Mumps, Rubella, and Varicella Vaccine, Live (ProQuad®), Pneumococcal 7-valent Conjugate Vaccine (Diphtheria CRM197, Prevnar), or Haemophilus B Conjugate Vaccine (Meningococcal Protein Conjugate, PedvaxHIB®). Overall, the race distribution of study subjects was as follows: 64.7% Caucasian; 15.7% Hispanic-American; 12.3% Black; 4.8% other; 1.4% Asian; and 1.1% Native American. The distribution of subjects by gender was 51.8% male and 48.2% female.

In an open-label clinical trial, 653 children 12 to 23 months of age were randomized to receive a first dose of VAQTA with ProQuad and Prevnar concomitantly (N=330) or a first dose of ProQuad and pneumococcal 7-valent conjugate vaccine concomitantly, followed by a first dose of VAQTA 6 weeks later (N=323). Approximately 6 months later, subjects received either the second doses of ProQuad and VAQTA concomitantly or the second doses of ProQuad and VAQTA separately. The race distribution of the study subjects was as follows: 60.3% Caucasian; 21.6% African-American; 9.5% Hispanic-American; 7.2% other; 1.1% Asian; and 0.3% Native American. The distribution of subjects by gender was 50.7% male and 49.3% female.

Table 1 presents rates of solicited local reactions at the VAQTA injection site and rates of elevated temperatures (≥100.4°F and ≥102.2°F) that occurred within 5 days following each dose of VAQTA and elevated temperatures >98.6°F for a total of 14 days after vaccination; occurrences of these events were recorded daily on diary cards. Table 2 presents rates of unsolicited systemic adverse events that occurred within 14 days at ≥5% in any group following each dose of VAQTA.

Table 1: Incidences of Solicited Local Adverse Reactions at the VAQTA Injection Site and Elevated Temperatures Following Each Dose of VAQTA in Healthy Children 12-23 Months of Age Receiving VAQTA Alone or Concomitantly With ProQuad and PREVNAR [Pneumococcal 7-valent Conjugate Vaccine]
 | Dose 1 |  | Dose 2
Adverse reaction: Days 1-5 unless noted | VAQTA alone | VAQTA + ProQuad + Prevnar concomitantly | VAQTA alone | VAQTA + ProQuad concomitantly
Injection site adverse reactions | N=274 | N=311 | N=251 | N=263
Injection site erythema | 11.7% | 9.6% | 12.7% | 9.5%
Injection site pain/tenderness | 15.3% | 20.9% | 20.3% | 17.5%
Injection site swelling | 9.5% | 6.8% | 7.6% | 6.1%
Temperature > 98.6°F or feverish (Days 1-14) | 12.4% | 35.7% | 10.8% | 10.3%
 | N=243 | N=285 | N=221 | N=237
Temperature ≥ 100.4°F | 10.3% | 16.8% | 10% | 4.2%
Temperature ≥ 102.2 °F | 2.1% | 3.5% | 2.3% | 2.5%
N=number of subjects for whom data are available.

Table 2: Incidences of Unsolicited Systemic Adverse Events ≥5% in Any Group Following Each Dose of VAQTA in Healthy Children 12-23 Months of Age Receiving VAQTA Alone or Concomitantly With ProQuad and PREVNAR [Pneumococcal 7-valent Conjugate Vaccine]
 | Dose 1 |  | Dose 2
Adverse Event: Days 1-14 | VAQTA alone | VAQTA + ProQuad + PREVNAR concomitantly | VAQTA alone | VAQTA + ProQuad concomitantly
 | N=274 | N=311 | N=251 | N=263
General Disorders and Administration Site Conditions
Irritability | 3.6% | 6.1% | 2.8% | 2.7%
Infections and Infestations
Upper respiratory tract infection | 3.3% | 6.1% | 4.8% | 5.7%
Skin and Subcutaneous Tissue Disorders
Dermatitis diaper | 1.1% | 6.1% | 2.4% | 3.4%

In Stage I of an open, multicenter, randomized study, children 15 months of age were randomized to receive the first dose of VAQTA alone (N=151) or concomitantly with PedvaxHIB and INFANRIX (N=155); another group of children 15 months of age were randomized to receive the first dose of VAQTA alone (N=152) or concomitantly with PedvaxHIB (N=159). All groups received the second dose of VAQTA alone at least 6 months following the first dose. The race distribution of Stage I study subjects was: 63.9% Caucasian; 17.5% Hispanic-American; 14.7% Black; 2.6% other; and 1.3% Asian. The distribution of subjects by gender was 54.0% male and 46.0% female. In Stage II of this study, an additional 654 children 12-17 months of age received the first dose of VAQTA alone followed by the second dose of VAQTA 6 months later. The race distribution of Stage II of the study subjects was: 66.1% Caucasian; 10.6% Hispanic-American; 16.8% Black; 4.7% other; and 1.5% Asian. The distribution of subjects by gender was 51.2% male and 48.8% female.

Table 3 presents rates of solicited local reactions at the VAQTA injection-site and rates of elevated temperatures (≥100.4°F and ≥102.2°F) that occurred within 5 days following each dose of VAQTA and elevated temperatures >98.6°F for a total of 14 days following each dose of VAQTA. Occurrences of these events were recorded daily on diary cards. Table 4 presents rates of unsolicited systemic adverse events that occurred within 14 days at ≥5% following each dose of VAQTA.

Table 3: Incidences of Solicited Local Adverse Reactions at the VAQTA Injection Site and Elevated Temperatures Following Each Dose of VAQTA in Healthy Children 12-23 Months of Age Receiving VAQTA Alone or Concomitantly with PedvaxHIB With or Without INFANRIX (Stage I) and those Receiving VAQTA Alone at Both Doses (Stage II)
 | Stage I |  |  | Stage II
 | Dose 1 |  | Dose 2 | Dose 1 | Dose 2
Adverse Reaction: Days 1-5 unless noted | VAQTA alone | VAQTA + PedvaxHIB and Infanrix or VAQTA + PedvaxHIB concomitantly | VAQTA alone | VAQTA alone | VAQTA alone
Injection site adverse reactions | N=256 | N=302 | N=503 | N=647 | N=599
Injection site erythema | 18.0% | 19.9% | 21.5% | 11.7% | 16.2%
Injection site pain/tenderness | 21.9% | 36.4% | 27.4% | 20.1% | 22.9%
Injection site swelling | 10.2% | 14.2% | 10.1% | 7.1% | 7.0%
Temperature > 98.6°F or feverish (Days 1-14) | 10.2% | 17.2% | 10.7% | 10.0% | 8.2%
 | N=234 | N=290 | N=473 | N=631 | N=591
Temperature ≥ 100.4°F | 9.0% | 16.9% | 9.1% | 9.4% | 8.6%
Temperature ≥ 102.2 °F | 3.8% | 3.1% | 3.2% | 2.9% | 2.4%
N= number of subjects for whom data is available

Table 4: Incidences of Unsolicited Systemic Adverse Events ≥5% in Any Group Following Each Dose of VAQTA in Healthy Children 12-23 Months of Age Receiving VAQTA Alone or Concomitantly with PedvaxHIB With or Without INFANRIX (Stage I) and Those Receiving VAQTA Alone at Both Doses (Stage II)
 | Stage I |  |  | Stage II
 | Dose 1 |  | Dose 2 | Dose 1 | Dose 2
Adverse Event: Days 1-14 | VAQTA alone | VAQTA + PedvaxHIB and Infanrix or VAQTA + PedvaxHIB concomitantly | VAQTA alone | VAQTA alone | VAQTA alone
 | N=256 | N=302 | N=503 | N=647 | N=599
Gastrointestinal Disorders
Diarrhea | 3.9% | 8.3% | 3.8% | 4.6% | 3.8%
Teething | 3.1% | 2.3% | 1.4% | 5.7% | 4.3%
General Disorders and Administration Site Conditions
Irritability | 6.3% | 9.6% | 4.0% | 8.8% | 6.5%
Infections and Infestations
Upper respiratory tract infection | 2.3% | 3.3% | 3.0% | 4.9% | 5.2%
Respiratory, Thoracic and Mediastinal Disorders
Rhinorrhea | 2.0% | 4.0% | 3.8% | 6.2% | 3.8%

Data presented in Tables 1 through 4 on solicited local reactions, and solicited and unsolicited systemic adverse events with incidence ≥5% following each dose of VAQTA are representative of other clinical trials of VAQTA in children 12 through 23 months of age. Across the five studies conducted in children 12-23 months of age, ≥39.9% of subjects experienced local adverse reactions and ≥55.7% of subjects experienced systemic adverse events. The majority of local and systemic adverse events were mild to moderate in intensity.

The following additional unsolicited local adverse reactions and systemic adverse events were observed at a common frequency of ≥1% to <10% in any individual clinical study. This listing includes only the adverse reactions not reported elsewhere in the label. These local adverse reactions and systemic adverse events occurred among recipients of VAQTA alone or VAQTA given concomitantly within 14 days following any dose of VAQTA across four clinical studies.

Eye disorders: Conjunctivitis
Gastrointestinal disorders: Constipation; vomiting
General disorders and administration site conditions: Injection-site bruising; injection-site ecchymosis
Infections and infestations: Otitis media; nasopharyngitis; rhinitis; viral infection; croup; pharyngitis streptococcal; laryngotracheobronchitis; viral exanthema; gastroenteritis viral; roseola
Metabolism and nutrition disorders: Anorexia
Psychiatric disorders: Insomnia; crying
Respiratory, thoracic and mediastinal disorders: Cough; nasal congestion; respiratory congestion
Skin and subcutaneous tissue disorders: Rash vesicular; measles-like/rubella-like rash; varicella-like rash; rash morbilliform

Serious Adverse Events (Children 12 through 23 Months of Age): Across the five studies conducted in subjects 12-23 months of age, 0.7% (32/4374) of subjects reported a serious adverse event following any dose of VAQTA, and 0.1% (5/4374) of subjects reported a serious adverse event judged to be vaccine related by the study investigator. The serious adverse events were collected over the period defined in each protocol (14, 28, or 42 days). Vaccine-related serious adverse events which occurred following any dose of VAQTA with or without concomitant vaccines included febrile seizure (0.05%), dehydration (0.02%), gastroenteritis (0.02%), and cellulitis (0.02%).

Children/Adolescents — 2 Years through 18 Years of Age

In 11 clinical trials, 2615 healthy children 2 years through 18 years of age received at least one dose of VAQTA. These studies included administration of VAQTA in varying doses and regimens (1377 children received one or more 25U doses). The race distribution of the study subjects who received at least one dose of VAQTA in these studies was as follows: 84.7% Caucasian; 10.6% American Indian; 2.3% African-American; 1.5% Hispanic-American; 0.6% other; 0.2% Oriental. The distribution of subjects by gender was 51.2% male and 48.8% female.

In a double-blind, placebo-controlled efficacy trial (i.e. The Monroe Efficacy Study), 1037 healthy children and adolescents 2 through 16 years of age were randomized to receive a primary dose of 25U of VAQTA and a booster dose of VAQTA 6, 12, or 18 months later, or placebo (alum diluent). All study subjects were Caucasian: 51.5% were male and 48.5% were female. Subjects were followed days 1 to 5 postvaccination for fever and local adverse reactions and days 1 to 14 for systemic adverse events. The most common adverse events/reactions were injection-site reactions, reported by 6.4% of subjects. Table 5 summarizes local adverse reactions and systemic adverse events reported in ≥1% of subjects. There were no significant differences in the rates of any adverse events or adverse reactions between vaccine and placebo recipients after Dose 1.

Table 5: Local Adverse Reactions and Systemic Adverse Events (≥1%) in Healthy Children and Adolescents from the Monroe Efficacy Study
Adverse Event | VAQTA (N=519) |  | Placebo (Alum Diluent) [No statistically significant differences between the two groups.] , [Second injection of placebo not administered because code for the trial was broken.] , [Placebo (Alum diluent) = amorphous aluminum hydroxyphosphate sulfate.] (N=518) Rate (Percent)
 | Dose 1 Rate (Percent) | Booster Rate (Percent) | Placebo (Alum Diluent) [No statistically significant differences between the two groups.] , [Second injection of placebo not administered because code for the trial was broken.] , [Placebo (Alum diluent) = amorphous aluminum hydroxyphosphate sulfate.] (N=518) Rate (Percent)
Injection Site [Adverse Reactions at the injection site (VAQTA) Days 1-5 after vaccination with VAQTA] | n=515 | n=475 | n=510
Pain | 6.4% | 3.4% | 6.3%
Tenderness | 4.9% | 1.7% | 6.1%
Erythema | 1.9% | 0.8% | 1.8%
Swelling | 1.7% | 1.5% | 1.6%
Warmth | 1.7% | 0.6% | 1.6%
Systemic [Systemic adverse events reported Days 1-15 after vaccination, regardless of causality.] | n=519 | n=475 | n=518
Abdominal pain | 1.2% | 1.1% | 1.0%
Pharyngitis | 1.2% | 0% | 0.8%
Headache | 0.4% | 0.8% | 1.0%
N=Number of subjects enrolled/randomized.
Percent=percentage of subjects for whom data are available with adverse event
n=number of subjects for whom adverse events available

Adults — 19 Years of Age and Older

In an open-label clinical trial, 240 healthy adults 18 to 54 years of age were randomized to receive either VAQTA (50U/1-mL) with Typhim Vi (Typhoid Vi polysaccharide vaccine) and YF-Vax (yellow fever vaccine) concomitantly (N=80), typhoid Vi polysaccharide and yellow fever vaccines concomitantly (N=80), or VAQTA alone (N=80). Approximately 6 months later, subjects who received VAQTA were administered a second dose of VAQTA. The race distribution of the study subjects who received VAQTA with or without typhoid Vi polysaccharide and yellow fever vaccine was as follows: 78.3% Caucasian; 14.2% Oriental; 3.3% other; 2.1% African-American; 1.7% Indian; 0.4% Hispanic-American. The distribution of subjects by gender was 40.8% male and 59.2% female. Subjects were monitored for local adverse reactions and fever for 5 days and systemic adverse events for 14 days after each vaccination. In the 14 days after the first dose of VAQTA, the proportion of subjects with adverse events was similar between recipients of VAQTA given concomitantly with typhoid Vi polysaccharide and yellow fever vaccines compared to recipients of typhoid Vi polysaccharide and yellow fever vaccines without VAQTA. Table 6 summarizes solicited local adverse reactions and Table 7 summarizes unsolicited systemic adverse events reported in ≥5% in adults who received one or two doses of VAQTA alone and for subjects who received VAQTA concomitantly with typhoid Vi polysaccharide and yellow fever vaccines. There were no solicited systemic complaints reported at a rate ≥5%. Fever ≥101°F occurred in 1.3% of subjects in each group.

Table 6: Incidences of Solicited Local Adverse Reactions in Healthy Adults ≥19 Years of Age Occurring at ≥5% After Any Dose
Adverse Event | VAQTA administered alone (N=80) | VAQTA + ViCPS [ViCPS=Typhoid Vi polysaccharide vaccine.] and Yellow Fever vaccines administered concomitantly [VAQTA administered concomitantly with typhoid Vi polysaccharide (ViCPS) and yellow fever vaccines.] (N=80)
Adverse Event | Rate (Percent)
Injection-site [Adverse Reactions at the injection site (VAQTA) Days 1-5 after vaccination]
Pain/tenderness/soreness | 78.8% | 70.3%
Warmth | 23.7% | 23.7%
Swelling | 16.2% | 8.8%
Erythema | 17.5% | 6.3%
N=Number of subjects enrolled/randomized.
Percent=percentage of subjects with adverse event.

Table 7: Incidences of Unsolicited Systemic Adverse Events in Adults ≥19 Years of Age Occurring at ≥5% After Any Dose
Body System | VAQTA administered alone (N=80) | VAQTA + ViCPS [ViCPS=Typhoid Vi polysaccharide vaccine.] and Yellow Fever vaccines administered concomitantly [VAQTA administered concomitantly with typhoid Vi polysaccharide (ViCPS) and yellow fever vaccines.] (N=80)
Adverse Event
 | Rate (Percent)
General disorders and administration site reactions [Systemic Adverse Events reported Days 1-15 after vaccination, regardless of causality.]
Asthenia/fatigue | 7.5% | 11.3%
Chills | 1.3% | 7.5%
Gastrointestinal disorders
Nausea | 7.5% | 12.5%
Musculoskeletal and connective tissue disorders
Myalgia | 5.0% | 10.0%
Arm pain | 0.0% | 6.3%
Nervous system disorders
Headache | 23.8% | 26.3%
Infections and infestations
Upper respiratory infection | 7.5% | 3.8%
Pharyngitis | 2.5% | 6.3%
N=Number of subjects enrolled/randomized with data available.
Percent=percentage of subjects with adverse event for whom data are available.

In four clinical trials involving 1645 healthy adults 19 years of age and older who received one or more 50U doses of hepatitis A vaccine, subjects were followed for fever and local adverse reactions 1 to 5 days postvaccination and for systemic adverse events 1 to 14 days postvaccination. One single-blind study evaluated doses of VAQTA with varying amounts of viral antigen and/or alum content in healthy adults ≥170 pounds and ≥30 years of age (N=210 adults administered 50U/1-mL dose). One open-label study evaluated VAQTA given with immune globulin (IG) or alone (N=164 adults who received VAQTA alone). A third study was single-blind and evaluated 3 different lots of VAQTA (N=1112). The fourth study that was also single-blind evaluated doses of VAQTA with varying amounts of viral antigen in healthy adults ≥170 pounds and ≥30 years of age (N=159 adults administered the 50U/1-mL dose). Overall, the race distribution of the study subjects who received at least one dose of VAQTA was as follows: 94.2% Caucasian; 2.2% Black; 1.5% Hispanic; 1.5% Oriental; 0.4% other; 0.2% American Indian. 47.6% of subjects were male and 52.4% were female. The most common adverse event/reaction was injection-site pain/soreness/tenderness reported by 67.0% of subjects. Of all reported injection-site reactions 99.8% were mild (i.e., easily tolerated with no medical intervention) or moderate (i.e., minimally interfered with usual activity possibly requiring little medical intervention). Listed below in Table 8 are the local adverse reactions and systemic adverse events reported by ≥5% of subjects, in decreasing order of frequency within each body system.

Table 8: Incidences of Local Adverse Reactions and Systemic Adverse Events ≥5% in Adults 19 Years of Age and Older
Body System | VAQTA (Any Dose) (N=1645)
Adverse Events | Rate (n/total n)
Nervous system disorders [Systemic Adverse Events reported Days 1 to 14 after vaccination, regardless of causality.] | n=1641
Headache | 16.1%
General disorders and administration site reactions [Adverse Reactions at the injection site (VAQTA) and measured fever Days 1 to 5 after vaccination.] | n=1640
Injection-site pain/tenderness/soreness | 67.0%
Injection-site warmth | 18.2%
Injection-site swelling | 14.7%
Injection-site erythema | 13.7%
N=Number of subjects enrolled/randomized.
n=Number of subjects in each category with data available.
Percent=percentage of subjects for whom data are available with adverse event.

The following additional unsolicited systemic adverse events were observed among recipients of VAQTA that occurred within 14 days at a common frequency of ≥1% to <10% following any dose not reported elsewhere in the label. These adverse reactions have been reported across 4 clinical studies.

Musculoskeletal and connective tissue disorders: Back pain; stiffness
Reproductive system and breast disorders: Menstruation disorders

6.2 Post-Marketing Experience

The following additional adverse events have been reported with use of the marketed vaccine. Because these reactions are reported voluntarily from a population of uncertain size, it is not possible to reliably estimate their frequency or establish a causal relationship to a vaccine exposure.

Blood and lymphatic disorders: Thrombocytopenia.
Nervous system disorders: Guillain-Barré syndrome; cerebellar ataxia; encephalitis.

Post-Marketing Observational Safety Study

In a post-marketing, 60-day safety surveillance study, conducted at a large health maintenance organization in the United States, a total of 42,110 individuals ≥2 years of age received 1 or 2 doses of VAQTA (13,735 children/adolescents and 28,375 adult subjects). Safety was passively monitored by electronic search of the automated medical records database for emergency room and outpatient visits, hospitalizations, and deaths. Medical charts were reviewed when an event was considered to be possibly vaccine-related by the investigator. None of the serious adverse events identified were assessed as being related to vaccine by the investigator. Diarrhea/gastroenteritis, resulting in outpatient visits, was determined by the investigator to be the only vaccine-related nonserious adverse reaction in the study. There was no vaccine-related adverse reaction identified that had not been reported in earlier clinical trials with VAQTA.

7 DRUG INTERACTIONS

7.1 Use with Other Vaccines

Do not mix VAQTA with any other vaccine in the same syringe or vial. Use separate injection sites and syringes for each vaccine. Please refer to package inserts of coadministered vaccines.

In clinical trials in children, VAQTA was concomitantly administered with one or more of the following US licensed vaccines: Measles, Mumps, and Rubella Virus Vaccine, Live; Varicella Vaccine, Live; Diphtheria and Tetanus Toxoids and Acellular Pertussis Vaccine, Adsorbed; Measles, Mumps, Rubella, and Varicella Vaccine, Live; Pneumococcal 7-valent Conjugate Vaccine (Diphtheria CRM197); and Haemophilus B Conjugate Vaccine (Meningococcal Protein Conjugate). Safety and immunogenicity were similar for concomitantly administered vaccines compared to separately administered vaccines.

In clinical trials in adults, VAQTA was concomitantly administered with typhoid Vi polysaccharide and yellow fever vaccines [see Adverse Reactions (6.1) and Clinical Studies (14.2, 14.7)]. Safety and immunogenicity were similar for concomitantly administered vaccines compared to separately administered vaccines.

7.2 Use with Immune Globulin

VAQTA may be administered concomitantly with Immune Globulin, human, using separate sites and syringes. The recommended vaccination regimen for VAQTA should be followed. Consult the manufacturer's product circular for the appropriate dosage of Immune Globulin. A booster dose of VAQTA should be administered at the appropriate time as outlined in the recommended regimen for VAQTA [see Clinical Studies (14.5)].

7.3 Immunosuppressive Therapy

If VAQTA is administered to a person receiving immunosuppressive therapy, an adequate immunologic response may not be obtained.

8 USE IN SPECIFIC POPULATIONS

8.1 Pregnancy

Risk Summary

All pregnancies have a risk of birth defect, loss, or other adverse outcomes. In the U.S. general population, the estimated background risk of major birth defects and miscarriage in clinically recognized pregnancies is 2% to 4% and 15% to 20%, respectively.

There are no adequate and well-controlled studies designed to evaluate VAQTA in pregnant women. Available post-approval data do not suggest an increased risk of miscarriage or major birth defects in women who received VAQTA during pregnancy.

Developmental toxicity studies have not been conducted with VAQTA in animals.

Data

Human Data

Post-approval adverse reactions are reported voluntarily from a population of uncertain size. It is not always possible to reliably estimate their frequency or establish a causal relationship to the vaccine.

In prospectively reported spontaneous post-approval reports from 1995 to 2018, 36 women with a known pregnancy outcome were exposed to VAQTA during pregnancy following the last menstrual period. After excluding induced abortions (n=4) and those with exposure in the third trimester (n=2), there were 30 pregnancies with known outcomes with exposures in the first or second trimester. Miscarriage was reported for 3 of 30 (10%) pregnancies. Major birth defects were reported for 1 of 27 (3.7%) live born infants. The rates of miscarriage and major birth defects were consistent with estimated background rates.

8.2 Lactation

Risk Summary

It is not known whether VAQTA is excreted in human milk. Data are not available to assess the effects of VAQTA on the breastfed infant or on milk production/excretion.

The developmental and health benefits of breastfeeding should be considered along with the mother's clinical need for VAQTA and any potential adverse effects on the breastfed child from VAQTA or from the underlying maternal condition. For preventive vaccines the underlying condition is susceptibility to disease prevented by the vaccine.

8.4 Pediatric Use

The safety of VAQTA has been evaluated in 4374 children 12 through 23 months of age, and 2615 children/adolescents 2 through 18 years of age who received at least one 25U dose of VAQTA [see Adverse Reactions (6) and Dosage and Administration (2)].

Safety and effectiveness in infants below 12 months of age have not been established.

8.5 Geriatric Use

In the post-marketing observational safety study which included 42,110 persons who received VAQTA [see Adverse Reactions (6.2)], 4769 persons were 65 years of age or older and 1073 persons were 75 years of age or older. There were no adverse events judged by the investigator to be vaccine-related in the geriatric study population. In other clinical studies, 68 subjects 65 years of age or older were vaccinated with VAQTA, 10 of whom were 75 years of age or older. No overall differences in safety and immunogenicity were observed between these subjects and younger subjects; however, greater sensitivity of some older individuals cannot be ruled out. Other reported clinical experience has not identified differences in responses between the elderly and younger subjects.

8.6 Immunocompromised Individuals

Immunocompromised persons may have a diminished immune response to VAQTA and may not be protected against HAV infection.

11 DESCRIPTION

VAQTA is an inactivated whole virus vaccine derived from hepatitis A virus grown in cell culture in human MRC-5 diploid fibroblasts. It contains inactivated virus of a strain which was originally derived by further serial passage of a proven attenuated strain. The virus is grown, harvested, purified by a combination of physical and high performance liquid chromatographic techniques developed at the Research Laboratories of Merck Sharp & Dohme LLC, Rahway, NJ, USA, formalin inactivated, and then adsorbed onto amorphous aluminum hydroxyphosphate sulfate.

VAQTA is a sterile suspension for intramuscular injection. One milliliter of the vaccine contains approximately 50U of hepatitis A virus antigen, which is purified and formulated without a preservative. Within the limits of current assay variability, the 50U dose of VAQTA contains less than 0.1 mcg of non-viral protein, less than 4 × 10^–6 mcg of DNA, less than 10^–4 mcg of bovine albumin, and less than 0.8 mcg of formaldehyde. Other process chemical residuals are less than 10 parts per billion (ppb), including neomycin.

Each 0.5-mL pediatric dose contains 25U of hepatitis A virus antigen and adsorbed onto approximately 0.225 mg of aluminum provided as amorphous aluminum hydroxyphosphate sulfate, and 35 mcg of sodium borate as a pH stabilizer, in 0.9% sodium chloride.

Each 1-mL adult dose contains 50U of hepatitis A virus antigen and adsorbed onto approximately 0.45 mg of aluminum provided as amorphous aluminum hydroxyphosphate sulfate, and 70 mcg of sodium borate as a pH stabilizer, in 0.9% sodium chloride.

12 CLINICAL PHARMACOLOGY

12.1 Mechanism of Action

VAQTA has been shown to elicit antibodies to hepatitis A as measured by ELISA.

Protection from hepatitis A disease has been shown to be related to the presence of antibody. However, the lowest titer needed to confer protection has not been determined.

13 NONCLINICAL TOXICOLOGY

13.1 Carcinogenesis, Mutagenesis, Impairment of Fertility

VAQTA has not been evaluated for its carcinogenic or mutagenic potential, or its potential to impair fertility. [See Use in Specific Populations (8).]

14 CLINICAL STUDIES

14.1 Efficacy of VAQTA: The Monroe Clinical Study

The immunogenicity and protective efficacy of VAQTA were evaluated in a randomized, double-blind, placebo-controlled study involving 1037 susceptible healthy children and adolescents 2 through 16 years of age in a U.S. community with recurrent outbreaks of hepatitis A (The Monroe Efficacy Study). All of these children were Caucasian, and there were 51.5% male and 48.5% female. Each child received an intramuscular dose of VAQTA (25U) (N=519) or placebo (alum diluent) (N=518). Among those individuals who were initially seronegative (measured by a modification of the HAVAB radioimmunoassay [RIA]), seroconversion was achieved in >99% of vaccine recipients within 4 weeks after vaccination. The onset of seroconversion following a single dose of VAQTA was shown to parallel the onset of protection against clinical hepatitis A disease.

Because of the long incubation period of the disease (approximately 20 to 50 days, or longer in children), clinical efficacy was based on confirmed cases [The clinical case definition included all of the following occurring at the same time: 1) one or more typical clinical signs or symptoms of hepatitis A (e.g., jaundice, malaise, fever ≥38.3°C); 2) elevation of hepatitis A IgM antibody (HAVAB-M); 3) elevation of alanine transferase (ALT) ≥2 times the upper limit of normal.] of hepatitis A occurring ≥50 days after vaccination in order to exclude any children incubating the infection before vaccination. In subjects who were initially seronegative, the protective efficacy of a single dose of VAQTA was observed to be 100% with 21 cases of clinically confirmed hepatitis A occurring in the placebo group and none in the vaccine group (p<0.001). The number of clinically confirmed cases of hepatitis A ≥30 days after vaccination were also compared. In this analysis, 28 cases of clinically confirmed hepatitis A occurred in the placebo group while none occurred in the vaccine group ≥30 days after vaccination. In addition, it was observed in this trial that no cases of clinically confirmed hepatitis A occurred in the vaccine group after day 16. [One vaccinee did not meet the pre-defined criteria for clinically confirmed hepatitis A but did have positive hepatitis A IgM and borderline liver enzyme (ALT) elevations on days 34, 50, and 58 after vaccination with mild clinical symptoms observed on days 49 and 50.] Following demonstration of protection with a single dose and termination of the study, a booster dose was administered to a subset of vaccinees 6, 12, or 18 months after the primary dose.

No cases of clinically confirmed hepatitis A disease ≥50 days after vaccination have occurred in those vaccinees from The Monroe Efficacy Study monitored for up to 9 years.

14.2 Other Clinical Studies

The efficacy of VAQTA in other age groups was based upon immunogenicity measured 4 to 6 weeks following vaccination. VAQTA was found to be immunogenic in all age groups.

Children — 12 through 23 Months of Age

In a clinical trial, children 12 through 23 months of age were randomized to receive the first dose of VAQTA with or without M-M-R II and VARIVAX (N=617) and the second dose of VAQTA with or without Tripedia and optionally either oral poliovirus vaccine (no longer licensed in the US) or IPOL (N=555). The race distribution of study subjects who received at least one dose of VAQTA was as follows: 56.7% Caucasian; 17.5% Hispanic-American; 14.3% African-American; 7.0% Native American; 3.4% other; 0.8% Oriental; 0.2% Asian; and 0.2% Indian. The distribution of subjects by gender was 53.6% male and 46.4% female. In the analysis population, there were 471 initially seronegative children 12 through 23 months of age, who received the first dose of VAQTA with (N=237) or without (N=234) M-M-R II and VARIVAX of whom 96% (95% CI: 93.7%, 97.5%) seroconverted (defined as having an anti-HAV titer ≥10 mIU/mL) post dose 1 with an anti-HAV geometric mean titer (GMT) of 48 mIU/mL (95% CI: 44.7, 51.6). There were 343 children in the analysis population who received the second dose of VAQTA with (N=168) or without (N=175) Tripedia and optional oral poliovirus vaccine or IPOL of whom 100% (95% CI: 99.3%, 100%) seroconverted post dose 2 with an anti-HAV GMT of 6920 mIU/mL (95% CI: 6136, 7801). Of children who received only VAQTA at both visits, 100% (n=97) seroconverted after the second dose of VAQTA.

In a clinical trial involving 653 healthy children 12 to 15 months of age, 330 were randomized to receive VAQTA, ProQuad, and pneumococcal 7-valent conjugate vaccine concomitantly, and 323 were randomized to receive ProQuad and pneumococcal 7-valent conjugate vaccine concomitantly followed by VAQTA 6 weeks later. The race distribution of the study subjects was as follows: 60.3% Caucasian; 21.6% African-American; 9.5% Hispanic-American; 7.2% other; 1.1% Asian/Pacific; and 0.3% Native American. The distribution of subjects by gender was 50.7% male and 49.3% female. In the analysis population, the seropositivity rate for hepatitis A antibody (defined as the percent of subjects with an anti-HAV titer ≥10 mIU/mL) was 100% (n=182; 95% CI: 98.0%, 100%) post dose 2 with an anti-HAV GMT of 4977 mIU/mL (95% CI: 4068, 6089) when VAQTA was given with ProQuad and pneumococcal 7-valent conjugate vaccine and 99.4% (n=159, 95% CI: 96.5%, 100%) post dose 2 with an anti-HAV GMT of 6123 mIU/mL (95% CI: 4826, 7770) when VAQTA alone was given. These seropositivity rates were similar whether VAQTA was administered with or without ProQuad and pneumococcal 7-valent conjugate vaccine.

In an open, multicenter, randomized study involving 617 children 15 months of age, 306 were randomized to receive VAQTA with or without PedvaxHIB and INFANRIX, and 311 were randomized to receive VAQTA with or without PedvaxHIB. The race distribution of the study subjects was as follows: 63.9% Caucasian; 17.5% Hispanic-American; 14.7% Black; 2.6% other; and 1.3% Asian. The distribution of subjects by gender was 54.0% male and 46.0% female. The seropositivity rate for hepatitis A antibody (defined as the percent of subjects with an anti-HAV titer ≥ 10 mIU/mL) 4 weeks post dose 2 was 100% (n=208, 95% CI: 98.2%, 100.0%) in those who received VAQTA concomitantly with PedvaxHIB and INFANRIX or concomitantly with PedvaxHIB. In those subjects who received VAQTA alone, the seropositivity rate for hepatitis A antibody was 100% (n=183, 95% CI: 98.0%, 100.0%), regardless of baseline hepatitis A serostatus. Overall, the anti-HAV GMT in the concomitant groups was 3616.5 mIU/mL (95% CI: 3084.5, 4240.2). The anti-HAV GMT in the nonconcomitant groups was 4712.6 mIU/mL (95% CI: 3996.8, 5556.8). Comparable responses were observed in both the initially seronegative and seropositive subjects.

In three combined clinical studies 1022 initially seronegative subjects received 2 doses of VAQTA alone or concomitantly with other vaccines. Of the seronegative subjects, 99.9% achieved an anti-HAV titer ≥10 mIU/mL (95% CI: 99.5%, 100%) and an anti-HAV GMT of 5392.1 mIU/mL (95% CI: 4996.5, 5819.0) 4 weeks following dose 2 of VAQTA.

Children/Adolescents — 2 Years through 18 Years of Age

Immunogenicity data were combined from eleven randomized clinical studies in children and adolescents 2 through 18 years of age who received VAQTA (25U/0.5 mL). These included administration of VAQTA in varying doses and regimens (N=404 received 25U/0.5 mL), the Monroe Efficacy Study (N=973), and comparison studies for process and formulation changes (N=1238). The race distribution of the study subjects who received at least one dose of VAQTA in these studies was as follows: 84.8% Caucasian; 10.6% American Indian; 2.3% African-American; 1.5% Hispanic-American; 0.6% other; 0.2% Oriental. The distribution of subjects by gender was 51.2% male and 48.8% female. The proportions of subjects who seroconverted 4 weeks after the first and second doses administered 6 months apart were 97% (n=1230; 95% CI: 96%, 98%) and 100% (n=1057; 95% CI: 99.5%, 100%) of subjects with anti-HAV GMTs of 43 mIU/mL (95% CI: 40, 45) and 10,077 mIU/mL (95% CI: 9394, 10,810), respectively.

Adults — 19 Years of Age and Older

Immunogenicity data were combined from five randomized clinical studies in adults 19 years of age and older who received VAQTA (50U/1-mL). One single-blind study evaluated doses of VAQTA with varying amounts of viral antigen and/or alum content in healthy adults ≥170 pounds and ≥30 years of age (N=208 adults administered 50U/1-mL dose). One open-label study evaluated VAQTA given with immune globulin or alone (N=164 adults who received VAQTA alone). A third study was single-blind and evaluated 3 different lots of VAQTA (N=1112). The fourth study was single-blind and evaluated doses of VAQTA with varying amounts of viral antigen in healthy adults ≥170 pounds and ≥30 years of age (N=159 adults administered the 50U/1-mL dose). The fifth study was an open-label study to evaluate various regimens for time of administration of the booster dose of VAQTA (6, 12, and 18 months post dose 1, N=354). The race distribution of the study subjects who received at least one dose of VAQTA in these studies was as follows: 93.2% Caucasian; 2.5% African-American; 2.1% Hispanic-American; 1.4% Oriental; 0.5% other; 0.3% American Indian. The distribution of subjects by gender was 44.8% male and 55.2% female. The proportion of subjects who seroconverted 4 weeks after the first and second doses administered 6 months apart was 95% (n=1411; 95% CI: 94%, 96%) and 99.9% (n=1244; 95% CI: 99.4%, 100%) with GMTs of 37 mIU/mL (95% CI: 35, 38) and 6013 mIU/mL (95% CI: 5592, 6467), respectively. Furthermore, at 2 weeks postvaccination, 69.2% (n=744; 95% CI: 65.7%, 72.5%) of adults seroconverted with an anti-HAV GMT of 16 mIU/mL after a single dose of VAQTA.

14.3 Timing of Booster Dose Administration

Children/Adolescents — 2 through 18 Years of Age

In the Monroe Efficacy Study, children were administered a second dose of VAQTA (25U/0.5 mL) 6, 12, or 18 months following the initial dose. For subjects who received both doses of VAQTA, the GMTs and proportions of subjects who seroconverted 4 weeks after the booster dose administered 6, 12, and 18 months after the first dose are presented in Table 9.

Table 9: Children/Adolescents from the Monroe Efficacy Study Seroconversion Rates (%) and Geometric Mean Titers (GMT) for Cohorts of Initially Seronegative Vaccinees at the Time of the Booster(25U) and 4 Weeks Later
Months Following Initial 25U Dose | Cohort [Blood samples were taken at prebooster and postbooster time points.] (n=960) 0 and 6 Months | Cohort (n=35) 0 and 12 Months | Cohort (n=39) 0 and 18 Months
 | Seroconversion Rate GMT (mIU/mL) (95% CI)
6 | 97% 107 (98, 117) | — | —
7 | 100% 10433 (9681, 11243) | — | —
12 | — | 91% 48 (33, 71) | —
13 | — | 100% 12308 (9337, 16226) | —
18 | — | — | 90% 50 (28, 89)
19 | — | — | 100% 9591 (7613, 12082)

Adults — 19 years of age and older

Among the 5 randomized clinical studies in adults 19 years of age and older described in Section 14.2, there were additional data in which a booster dose of VAQTA (50U/1-mL) was administered 12 or 18 months after the first dose. For subjects in these studies who received both doses of VAQTA, the proportions who seroconverted 4 weeks after the booster dose administered 6, 12, and 18 months after the first dose were 100% of 1201 subjects, 98% of 91 subjects, and 100% of 84 subjects, respectively. GMTs in mIU/mL one month after the subjects received the booster dose at 6, 12, or 18 months after the primary dose were 5987 mIU/mL (95% CI: 5561, 6445), 4896 mIU/mL (95% CI: 3589, 6679), and 6043 mIU/mL (95% CI: 4687, 7793), respectively.

14.4 Duration of Immune Response

In follow-up of subjects in The Monroe Efficacy Study, in children (≥2 years of age) and adolescents who received two doses (25U) of VAQTA, detectable levels of anti-HAV antibodies (≥10 mIU/mL) were present in 100% of subjects for at least 10 years postvaccination. In subjects who received VAQTA at 0 and 6 months, the GMT was 819 mIU/mL (n=175) at 2.5 to 3.5 years and 505 mIU/mL (n=174) at 5 to 6 years, and 574 mIU/mL (n=114) at 10 years postvaccination. In subjects who received VAQTA at 0 and 12 months, the GMT was 2224 mIU/mL (n=49) at 2.5 to 3.5 years, 1191 mIU/mL (n=47) at 5 to 6 years, and 1005 mIU/mL (n=36) at 10 years postvaccination. In subjects who received VAQTA at 0 and 18 months, the GMT was 2501 mIU/mL (n=53) at 2.5 to 3.5 years, 1614 mIU/mL (n=56) at 5 to 6 years, and 1507 mIU/mL (n=41) at 10 years postvaccination.

In adults that were administered VAQTA at 0 and 6 months, the hepatitis A antibody response to date has been shown to persist at least 6 years. Detectable levels of anti-HAV antibodies (≥10 mIU/mL) were present in 100% (378/378) of subjects with a GMT of 1734 mIU/mL at 1 year, 99.2% (252/254) of subjects with a GMT of 687 mIU/mL at 2 to 3 years, 99.1% (219/221) of subjects with a GMT of 605 mIU/mL at 4 years, and 99.4% (170/171) of subjects with a GMT of 684 mIU/mL at 6 years postvaccination.

The total duration of the protective effect of VAQTA in healthy vaccinees is unknown at present.

14.5 Concomitant Administration of VAQTA and Immune Globulin

The concurrent use of VAQTA (50U) and immune globulin (IG, 0.06 mL/kg) was evaluated in an open-label, randomized clinical study involving 294 healthy adults 18 to 39 years of age. Adults were randomized to receive 2 doses of VAQTA 24 weeks apart (N=129), the first dose of VAQTA concomitant with a dose of IG followed by the second dose of VAQTA alone 24 weeks later (N=135), or IG alone (N=30). The race distribution of the study subjects who received at least one dose of VAQTA or IG in this study was as follows: 92.3% Caucasian; 4.0% Hispanic-American; 3.0% African-American; 0.3% Native American; 0.3% Asian/Pacific. The distribution of subjects by gender was 28.7% male and 71.3% female. Table 10 provides seroconversion rates and GMTs at 4 and 24 weeks after the first dose in each treatment group and at one month after a booster dose of VAQTA (administered at 24 weeks) [see Drug Interactions (7.2)].

Table 10: Seroconversion Rates (%) and Geometric Mean Titers (GMT) After Vaccination with VAQTA Plus IG, VAQTA Alone, and IG Alone
 | VAQTA plus IG | VAQTA | IG
Weeks | Seroconversion Rate GMT (mIU/mL) (95% CI)
4 | 100% 42 (39, 45) (n=129) | 96% 38 (33, 42) (n=135) | 87% 19 (15, 23) (n=30)
24 | 92% 83 (65, 105) (n=125) | 97% [The seroconversion rate and the GMT in the group receiving VAQTA alone were significantly higher than in the group receiving VAQTA plus IG (p=0.05, p<0.001, respectively).] 137 (112, 169) (n=132) | 0% Undetectable [Undetectable is defined as <10mIU/mL.] (n=28)
28 | 100% 4872 (3716, 6388) (n=114) | 100% 6498 (5111, 8261) (n=128) | N/A
N/A = Not Applicable.

14.6 Interchangeability of the Booster Dose

A randomized, double-blind clinical study in 537 healthy adults, 18 to 83 years of age, evaluated the immune response to a booster dose of VAQTA and HAVRIX given at 6 or 12 months following an initial dose of HAVRIX. Subjects were randomized to receive VAQTA (50U) as a booster dose 6 months (N=232) or 12 months (N=124) following an initial dose of HAVRIX or HAVRIX (1440 EL. U) as a booster dose 6 months (N=118) or 12 months (N=63) following an initial dose of HAVRIX. The race distribution of the study subjects who received the booster dose of VAQTA or HAVRIX in this study was as follows: 87.2% Caucasian; 8.0% African-American; 1.9% Hispanic-American; 1.3% Oriental; 0.9% Asian; 0.4% Indian; 0.4% other. The distribution of subjects by gender was 44.9% male and 55.1% female. When VAQTA was given as a booster dose following HAVRIX, the vaccine produced an adequate immune response (see Table 11) [see Dosage and Administration (2.1)].

Table 11: Seropositivity Rate, Booster Response Rate [Booster Response Rate is defined as greater than or equal to a tenfold rise from prebooster to postbooster titer and postbooster titer ≥100 mIU/mL.] and Geometric Mean Titer 4 Weeks Following a Booster Dose of VAQTA or HAVRIX Administered 6 to 12 Months After First Dose of HAVRIX [Study conducted in adults 18 years of age and older.]
First Dose | Booster Dose | Seropositivity Rate | Booster Response Rate | Geometric Mean Titer
HAVRIX 1440 EL.U. | VAQTA 50 U | 99.7% (n=313) | 86.1% (n=310) | 3272 (n=313)
HAVRIX 1440 EL.U. | HAVRIX 1440 EL.U. | 99.3% (n=151) | 80.1% (n=151) | 2423 (n=151)

14.7 Immune Response to Concomitantly Administered Vaccines

Clinical Studies of VAQTA with M-M-R II, VARIVAX, and Tripedia

In the clinical trial in which children 12 months of age received the first dose of VAQTA concomitantly with M-M-R II and VARIVAX described in Section 14.2, rates of seroprotection to hepatitis A were similar between the two groups who received VAQTA with or without M-M-R II and VARIVAX. Measles, mumps, and rubella immune responses were tested in 241 subjects, 263 subjects, and 270 subjects, respectively. Seropositivity rates were 98.8% [95% CI: 96.4%, 99.7%] for measles, 99.6% [95% CI: 97.9%, 100%] for mumps, and 100% [95% CI: 98.6%, 100%] for rubella, which were similar to observed historical rates (seropositivity rates 99% for all three antigens, with lower bound of the 95% CI >89%) following vaccination with a first dose of M-M-R II in this age group. Data from this study were insufficient to adequately assess the immune response to VARIVAX administered concomitantly with VAQTA. In this same study, the second dose of VAQTA at 18 months of age was given with or without Tripedia (DTaP). Seropositivity rates for diphtheria and tetanus were similar to those in historical controls. However, data from this study were insufficient to assess the pertussis response of DTaP when administered with VAQTA. Rates of seroprotection to hepatitis A were similar between the two groups who received VAQTA with or without M-M-R II and VARIVAX, and between the two groups who received VAQTA with or without DTaP.

Clinical Studies of VAQTA with ProQuad and Prevnar

In the clinical trial of concomitant use of VAQTA with ProQuad and pneumococcal 7-valent conjugate vaccine in children 12 to 15 months of age described in Section 14.2, the antibody GMTs for S. pneumoniae types 4, 6B, 9V, 14, 18C, 19F, and 23F 6 weeks after vaccination with pneumococcal 7-valent conjugate vaccine administered concomitantly with ProQuad and VAQTA were non-inferior as compared to GMTs observed in the group given pneumococcal 7-valent conjugate vaccine with ProQuad alone (the lower bounds of the 95% CI around the fold-difference for the 7 serotypes excluded 0.5). For the varicella component of ProQuad, in subjects with baseline antibody titers <1.25 gpELISA units/mL, the proportion with a titer ≥5 gpELISA units/mL 6 weeks after their first dose of ProQuad was non-inferior (defined as -10 percentage point change) when ProQuad was administered with VAQTA and pneumococcal 7-valent conjugate vaccine as compared to the proportion with a titer ≥5 gpELISA units/mL when ProQuad was administered with pneumococcal 7-valent conjugate vaccine alone (difference in seroprotection rate -5.1% [95% CI: -9.3, -1.4%]). Hepatitis A responses were similar when compared between the two groups who received VAQTA with or without ProQuad and pneumococcal 7-valent conjugate vaccine. Seroconversion rates and antibody titers for varicella and S. pneumoniae types 4, 6B, 9V, 14, 18C, 19F, and 23F were similar between groups at 6 weeks postvaccination.

Clinical Studies of VAQTA with INFANRIX and PedvaxHIB

In the clinical trial of concomitant administration of VAQTA with INFANRIX and PedvaxHIB in children 15 months of age, described in Section 14.2, when the first dose of VAQTA was administered concomitantly with either INFANRIX and PedvaxHIB or PedvaxHIB, there was no interference in immune response to hepatitis A as measured by seropositivity rates after dose 2 of VAQTA compared to administration of both doses of VAQTA alone. When dose 1 of VAQTA was administered concomitantly with either PedvaxHIB and INFANRIX or PedvaxHIB, there was no interference in immune response to Haemophilus influenzae b (as measured by the proportion of subjects who attained an anti-polyribosylribitol phosphate antibody titer >1.0 mcg/mL at 4 weeks after vaccination), compared to subjects receiving either PedvaxHIB and INFANRIX or PedvaxHIB. When VAQTA was administered concomitantly with INFANRIX and PedvaxHIB, there was no interference in immune responses at 4 weeks after vaccination to the pertussis antigens (PT, FHA, or pertactin, as measured by GMTs) and no interference in immune responses to diphtheria toxoid or tetanus toxoid (as measured by the proportion of subjects achieving an antibody titer >0.1 IU/mL) compared to administration of INFANRIX and PedvaxHIB.

Clinical Studies of VAQTA with Typhoid Vi Polysaccharide Vaccine and Yellow Fever Vaccine, Live Attenuated

In the clinical trial of concomitant use of VAQTA with typhoid Vi polysaccharide and yellow fever vaccines in adults 18-54 years of age described in Section 6.1, the antibody response rates for typhoid Vi polysaccharide and yellow fever were adequate when typhoid Vi polysaccharide and yellow fever vaccines were administered concomitantly with (N=80) and nonconcomitantly without VAQTA (N=80). The seropositivity rate for hepatitis A when VAQTA, typhoid Vi polysaccharide, and yellow fever vaccines were administered concomitantly was generally similar to when VAQTA was given alone [see Drug Interactions (7.1)].

Data are insufficient to assess the immune response to VAQTA and poliovirus vaccine when administered concomitantly.

16 HOW SUPPLIED/STORAGE AND HANDLING

VAQTA is available in single-dose vials and prefilled Luer-Lok® syringes.

Pediatric/Adolescent Formulations

25U/0.5 mL in single-dose vials and prefilled Luer-Lok® syringes.
NDC 0006-4831-41 – box of ten 0.5-mL single dose vials.
NDC 0006-4095-02 – carton of ten 0.5-mL prefilled single-dose Luer-Lok® syringes with tip caps.

Adult Formulations

50U/1-mL in single-dose vials and prefilled Luer-Lok® syringes.
NDC 0006-4841-00 – 1-mL single dose vial.
NDC 0006-4841-41 – box of ten 1-mL single dose vials.
NDC 0006-4096-02 – carton of ten 1-mL prefilled single-dose Luer-Lok® syringes with tip caps.

STORAGE AND HANDLING

Store vaccine at 2-8°C (36-46°F).
DO NOT FREEZE since freezing destroys potency.

17 PATIENT COUNSELING INFORMATION

Advise the patient to read the FDA-approved patient labeling (Patient Information).

Information for Vaccine Recipients and Parents or Guardians

- Inform the patient, parent or guardian of the potential benefits and risks of the vaccine.
- Question the vaccine recipient, parent, or guardian about the occurrence of any symptoms and/or signs of an adverse reaction after a previous dose of hepatitis A vaccine.
- Inform the patient, parent, or guardian about the potential for adverse events that have been temporally associated with administration of VAQTA.
- Tell the patient, parent, or guardian accompanying the recipient, to report adverse events to the physician or clinic where the vaccine was administered.
- Prior to vaccination, give the patient, parent, or guardian the Vaccine Information Statements which are required by the National Childhood Vaccine Injury Act of 1986. These materials are available free of charge at the Centers for Disease Control and Prevention (CDC) website (www.cdc.gov/vaccines).
- Tell the patient, parent, or guardian that the United States Department of Health and Human Services has established a Vaccine Adverse Event Reporting System (VAERS) to accept all reports of suspected adverse events after the administration of any vaccine, including but not limited to the reporting of events required by the National Childhood Vaccine Injury Act of 1986. The VAERS toll-free number is 1-800-822-7967. Reporting forms may also be obtained at the VAERS website at (www.//vaers.hhs.gov/).

Manuf. and Dist. by: Merck Sharp & Dohme LLC
Rahway, NJ 07065, USA

For patent information: www.msd.com/research/patent

The trademarks depicted herein are owned by their respective companies.

Copyright ©1996-2025 Merck & Co., Inc., Rahway, NJ, USA, and its affiliates.
All rights reserved.

uspi-v251-i-2509r021

Patient Information
VAQTA® (pronounced “vac-ta”)
(Hepatitis A Vaccine, Purified Inactivated)

This is a summary of information about VAQTA®. Read this information carefully before you or your child receives each dose of VAQTA. If you have any questions about VAQTA after reading this leaflet, you should ask your doctor. This information does not take the place of talking about VAQTA with your doctor or healthcare provider.

What is VAQTA?

- VAQTA is a vaccine that helps prevent Hepatitis A. Hepatitis A is an infection of the liver.
- It is a vaccine for people 12 months of age and older.

What do you need to know about VAQTA?

- You cannot get Hepatitis A from VAQTA.
- VAQTA will not prevent other types of Hepatitis, such as Hepatitis B.
- VAQTA may not be effective in everyone who gets the shot.
- VAQTA is not a treatment for those who already have Hepatitis A.

Who should not get VAQTA?

Do not get VAQTA if you or your child:

- have had an allergic reaction to any ingredients of VAQTA, including neomycin. (See section titled “What is in VAQTA?” at the end of this leaflet.)
- have had an allergic reaction to a previous dose of any Hepatitis A vaccine.

What should you tell the doctor or healthcare provider before getting VAQTA?

Tell your doctor or healthcare provider if you or your child:

- are allergic to latex. The vial stopper contains dry natural latex rubber. Latex may cause severe allergic reactions in some people.
- are pregnant or planning to get pregnant.
- are breast-feeding.
- have immune problems, like HIV or cancer.

If you have already gotten a Hepatitis A shot, talk to your doctor or healthcare provider to see if VAQTA is right for you.

The doctor will help decide if you or your child should get the shot.

What are the possible side effects of VAQTA?

The most common side effects seen with VAQTA are:

- pain, soreness, redness, swelling, and warmth where you or your child got the shot
- headache (adults 19 years and older)
- fever (children 12 to 23 months)

If you or your child have any of the following problems, tell your doctor right away because these may be signs of an allergic reaction:

- trouble breathing
- wheezing
- hives
- rash

If you or your child has any side effects that worry you or seem to get worse, tell your doctor or healthcare provider right away.

There may be other side effects that are not listed. For more information, ask your doctor or healthcare provider.

You may report any side effects to your or your child’s doctor or directly to the Vaccine Adverse Event Reporting System (VAERS) at 1-800-822-7967 or www.vaers.hhs.gov, or to Merck Sharp & Dohme LLC at 1-877-888-4231.

How is VAQTA given?

- It is a shot given in the arm or thigh.
- VAQTA is given in two doses on two different dates.
  - the 1st shot is given any time after 12 months of age.
  - the 2nd shot is given 6-18 months after the first shot.
- If you miss the 2nd shot or if you get your 2nd shot too soon, talk to your doctor or healthcare provider. They will decide what to do.

- How much VAQTA is given?
  - Children/Adolescents - 12 months through 18 years of age (0.5 mL dose)
  - Adults -19 years of age and older (1.0 mL dose)

What is in VAQTA?

Active ingredient: Hepatitis A virus, Inactivated.

Other ingredients: Aluminum hydroxyphosphate sulphate, sodium borate, sodium chloride, water.

This vaccine contains a trace amount of neomycin.

The vial stopper contains natural latex rubber.

VAQTA does not have any preservatives in it.

For more information, ask your doctor or healthcare provider. Keep this information in case you have questions later.

Manuf. and Dist. by: Merck Sharp & Dohme LLC
Rahway, NJ 07065, USA

For patent information: www.msd.com/research/patent

Copyright © 2006-2025 Merck & Co., Inc., Rahway, NJ, USA, and its affiliates.
All rights reserved.

usppi-v251-i-2509r002

This Patient Information has been approved by the U.S. Food and Drug Administration.

Revised: 09/2025

PRINCIPAL DISPLAY PANEL - 0.5 mL Vials Carton

NDC 0006-4831-41
10 Single-dose ~25U/0.5-mL Vials

(HEPATITIS A VACCINE, INACTIVATED)
VAQTA®
PEDIATRIC/ADOLESCENT

0.5 mL vial contains approximately 25U of hepatitis A virus antigen on an Amorphous aluminum
hydroxyphosphate sulfate adjuvant. Hepatitis A virus is grown in cell culture in human MRC-5
diploid fibroblasts.

Rx only

PRINCIPAL DISPLAY PANEL - 0.5 mL Syringes Carton

NDC 0006-4095-02
10 Single-Dose 0.5-mL Syringes

[HEPATITIS A VACCINE,
INACTIVATED]
VAQTA®

PEDIATRIC/ADOLESCENT
FORMULATION

This package contains 10 single-dose syringes.
Each 0.5-mL syringe contains approximately 25U of hepatitis A virus antigen
on an amorphous aluminum hydroxyphosphate sulfate adjuvant.

Hepatitis A virus is grown in cell culture in human MRC-5 diploid fibroblasts.

Rx only

PRINCIPAL DISPLAY PANEL - 1 mL Vials Carton

NDC 0006-4841-41
10 Single-dose
~50U/1-mL Vials

(HEPATITIS A VACCINE, INACTIVATED)
VAQTA®
ADULT FORMULATION

1 mL vial contains approximately 50U of hepatitis A virus antigen on an Amorphous aluminum
hydroxyphosphate sulfate adjuvant. Hepatitis A virus is grown in cell culture in human MRC-5
diploid fibroblasts.

Rx only

PRINCIPAL DISPLAY PANEL - 1 mL Syringes Carton

NDC 0006-4096-02
10 Single-Dose 1-mL Syringes

[HEPATITIS A VACCINE,
INACTIVATED]
VAQTA®

ADULT FORMULATION

This package contains 10 single-dose syringes.
Each 1-mL syringe contains approximately 50U of hepatitis A virus antigen
on an amorphous aluminum hydroxyphosphate sulfate adjuvant.

Hepatitis A virus is grown in cell culture in human MRC-5 diploid fibroblasts.

Rx only

PRINCIPAL DISPLAY PANEL - 1 mL Vial Carton

NDC 0006-4841-00
1 Single-dose
~50U/1-mL Vial

(HEPATITIS A
VACCINE,
INACTIVATED)
VAQTA®

ADULT
FORMULATION

1 mL contains approximately 50U
of hepatitis A virus antigen on an
Amorphous aluminum hydroxyphos-
phate sulfate adjuvant.

Hepatitis A virus is grown in cell
culture in human MRC-5 diploid
fibroblasts.

Rx only